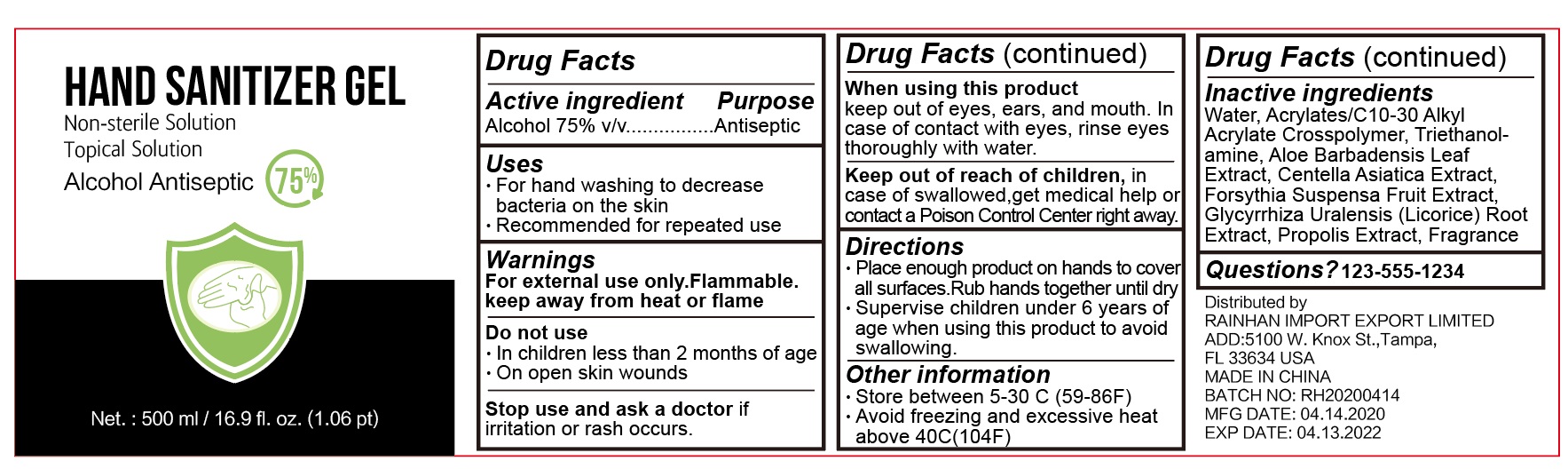 DRUG LABEL: Hand Sanitizer Gel
NDC: 77314-688 | Form: GEL
Manufacturer: Guangzhou Chuyu Cosmetics Co., Ltd.
Category: otc | Type: HUMAN OTC DRUG LABEL
Date: 20200513

ACTIVE INGREDIENTS: ALCOHOL 75 mL/100 mL
INACTIVE INGREDIENTS: ALOE VERA LEAF; CENTELLA ASIATICA; GLYCYRRHIZA URALENSIS ROOT; FORSYTHIA SUSPENSA FRUIT; WATER; PROPOLIS WAX; (C10-C30)ALKYL METHACRYLATE ESTER; TROLAMINE

Active ingredient

Alcohol 75% v/v (ethanol)

Purpose

Antiseptic

Uses

- For hand washing to decrease bacteria on the skin
- Recommended for repeated use

Warnings

For external use only. Flammable. Keep away from heat or flame

Do not use

- In children less than 2 months of age
- On open skin wounds

Stop use and ask a doctor

if irritation or rash occurs.

When using this product keep out of eyes, ears, and mouth. In case of contact with eyes, rinse eyes thoroughly with water.

Keep out of reach of children,

in case of swallowed,get medical help or contact a Poison Control Center right away.

Directions

- Place enough product on hands to cover all surfaces.Rub hands together until dry.
- Supervise children under 6 years of age when using this product to avoid swallowing.

Other information

- Store between 5-30 C (59-86F)
- Avoid freeezing and excessive heat above 40C (104F)

Inactive ingredients

Water, Acrylates/C10-30 Alkyl Acrylate Crosspolymer, Triethanolamine, Aloe Barbadensis Leaf Extract, Centella Asiatice Extract, Forsythia Suspensa Fruit Extract, Glycyrrhiza Uralensis (Licorice) Root Extract, Propolis Extract, Fragrance

Questions?

Questions? 123-555-1234